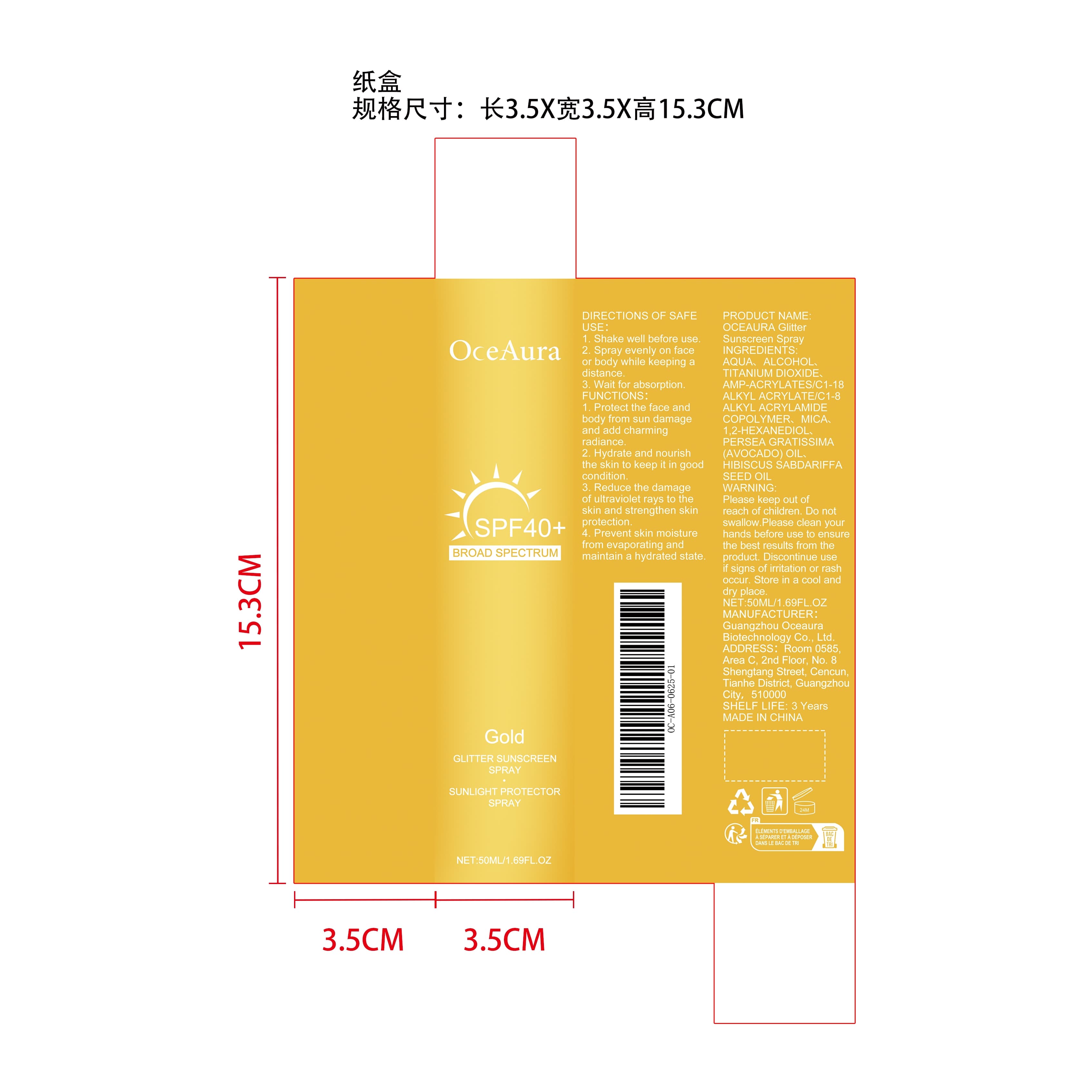 DRUG LABEL: OCEAURA Glitter Sunscreen
NDC: 85064-020 | Form: LIQUID
Manufacturer: Guangzhou Oceaura Biotechnology Co., Ltd.
Category: otc | Type: HUMAN OTC DRUG LABEL
Date: 20251128

ACTIVE INGREDIENTS: PERSEA GRATISSIMA (AVOCADO) OIL 0.01 mg/50 mg; HIBISCUS SABDARIFFA SEED OIL 0.01 mg/50 mg
INACTIVE INGREDIENTS: TITANIUM DIOXIDE 5 mg/50 mg; 1,2-HEXANEDIOL 0.1 mg/50 mg; AQUA 29.38 mg/50 mg; ALCOHOL 15 mg/50 mg; STYRENE/ACRYLAMIDE COPOLYMER (MW 500000) 0.4 mg/50 mg; MICA 0.1 mg/50 mg

ACTIVE INGREDIENT

PERSEA GRATISSIMA (AVOCADO) OIL、HIBISCUS SABDARIFFA SEED OIL

PURPOSE

1. Protect the face and body from sun damage and add charming radiance.

2. Hydrate and nourish the skin to keep it in good condition.

3. Reduce the damage of ultraviolet rays to the skin and strengthen skin protection.

4. Prevent skin moisture from evaporating and maintain a hydrated state.

WHEN USING

1. Shake well before use.

2. Spray evenly on face or body while keeping a distance.

3. Wait for absorption.

WARNINGS

Please keep out of reach of children. Do not swallow.Please clean your hands before use to ensure the best results from the product. Discontinue use if signs of irritation or rash occur. Store in a cool and dry place.

DO NOT USE

Discontinue use if signs of irritation or rash occur.

STOP USE

Discontinue use if signs of irritation or rash occur.

KEEP OUT OF REACH OF CHILDREN

Please keep out of reach of children. Do not swallow.

STORAGE AND HANDLING

Store in a cool and dry place.

INACTIVE INGREDIENT

AQUA、ALCOHOL、TITANIUM DIOXIDE、AMP-ACRYLATES/C1-18 ALKYL ACRYLATE/C1-8 ALKYL ACRYLAMIDE COPOLYMER、MICA、1,2-HEXANEDIOL

INDICATIONS AND USAGE

1. Shake well before use.

2. Spray evenly on face or body while keeping a distance.

3. Wait for absorption.

DOSAGE AND ADMINISTRATION

1. Shake well before use.

2. Spray evenly on face or body while keeping a distance.

3. Wait for absorption.